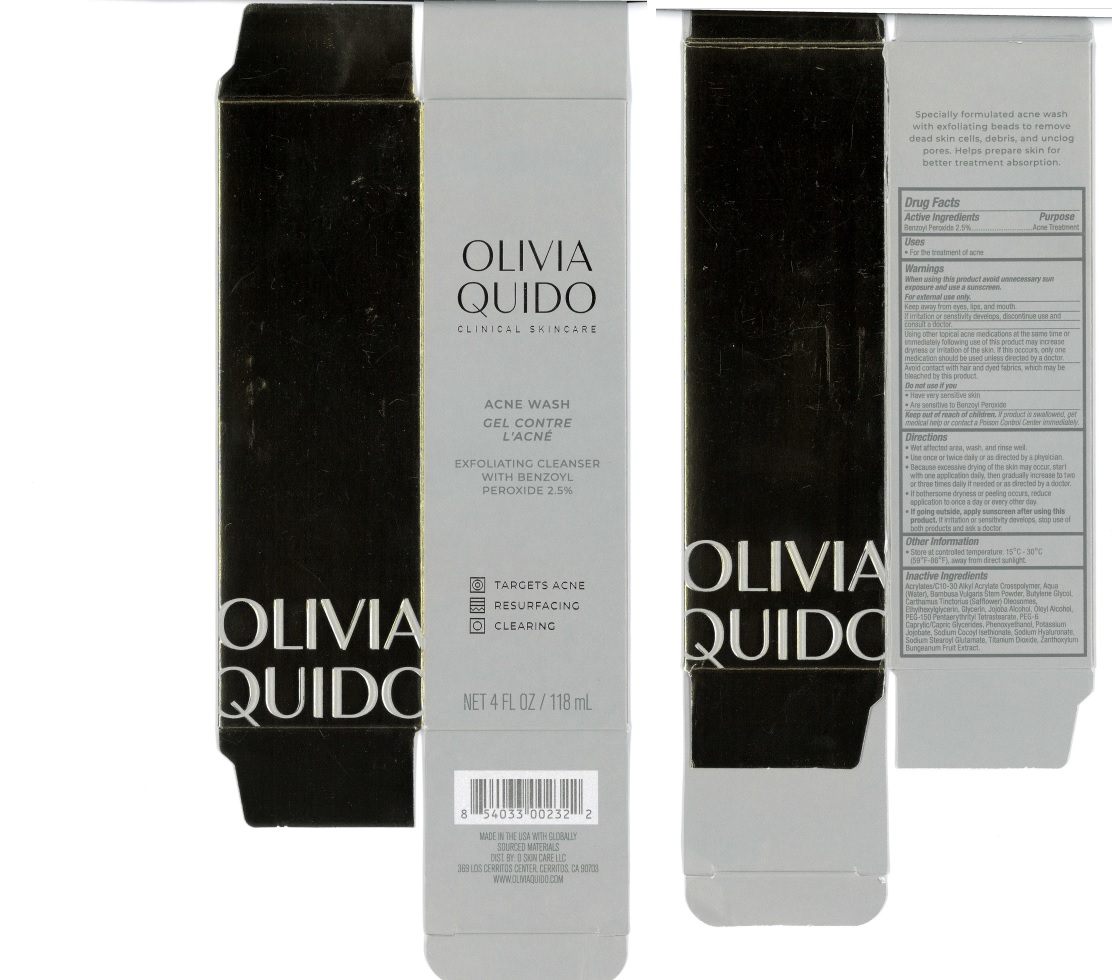 DRUG LABEL: Olivia Quido Acne Wash
NDC: 71421-901 | Form: LIQUID
Manufacturer: O Skin Care LLC
Category: otc | Type: HUMAN OTC DRUG LABEL
Date: 20240901

ACTIVE INGREDIENTS: BENZOYL PEROXIDE 2.5 g/100 g
INACTIVE INGREDIENTS: PHENOXYETHANOL; SODIUM COCOYL ISETHIONATE; ACRYLATES/C10-30 ALKYL ACRYLATE CROSSPOLYMER (60000 MPA.S); ETHYLHEXYLGLYCERIN; SODIUM STEAROYL GLUTAMATE; TITANIUM DIOXIDE; BUTYLENE GLYCOL; WATER; CARTHAMUS TINCTORIUS (SAFFLOWER) OLEOSOMES; GLYCERIN; ZANTHOXYLUM BUNGEANUM FRUIT; PEG-150 PENTAERYTHRITYL TETRASTEARATE; BAMBUSA VULGARIS STEM; OLEYL ALCOHOL; PEG-6 CAPRYLIC/CAPRIC GLYCERIDES; HYALURONATE SODIUM

Olivia Quido Acne Wash

ACTIVE INGREDIENT

Benzoyl Peroxide 2.5%

PURPOSE

Acne Treatment

Uses

For the treatment of acne

Warnings

When using this product avoid unnecessary sun exposure and use a sunscreen.

Keep away from eyes, lips, and mouth.

Using other topical acne medications at the same time or immediately following use of this product may increase dryness or irritation of the skin. If this occcurs, only one medication should be used unless directed by a doctor. Avoid contact with hair and dyed fabrics, which may be bleached by this product.

Do not use if you

• Have very sensitive skin
• Are sensitive to Benzoyl Peroxide

Keep out of reach of children

If product is swallowed, get medical help or contact a Poison Control Center immediately.

Directions

• Wet affected area, wash, and rinse well.
• Use once or twice daily or as directed by a physician.

INDICATIONS AND USAGE

• Because excessive drying of the skin may occur, start with one application daily, then gradually increase to two or three times daily if needed or as directed by a doctor.
• If bothersome dryness or peeling occurs, reduce application to once a day or every other day.
• If going outside, apply sunscreen after using this product. If irritation or sensitivity develops, stop use of both products and ask a doctor.

Inactive Ingredients

Acrylates/C10-30 Alkyl Acrylate Crosspolymer, Aqua (Water), Bambusa Vulgaris Stem Powder, Butylene Glycol, Carthamus Tinctorius (Safflower) Oleosomes, Ethylhexylglycerin, Glycerin, Jojoba Alcohol, Oleyl Alcohol, PEG-150 Pentaerythrityl Tetrastearate, PEG-6 Caprylic/Capric Glycerides, Phenoxyethanol, Potassium Jojobate, Sodium Cocoyl Isethionate, Sodium Hyaluronate, Sodium Stearoyl Glutamate, Titanium Dioxide, Zanthoxylum Bungeanum Fruit Extract.

Other Information

Store at controlled temperature: 15°C -30°C
(59°F-86°F), away direct sunlight.